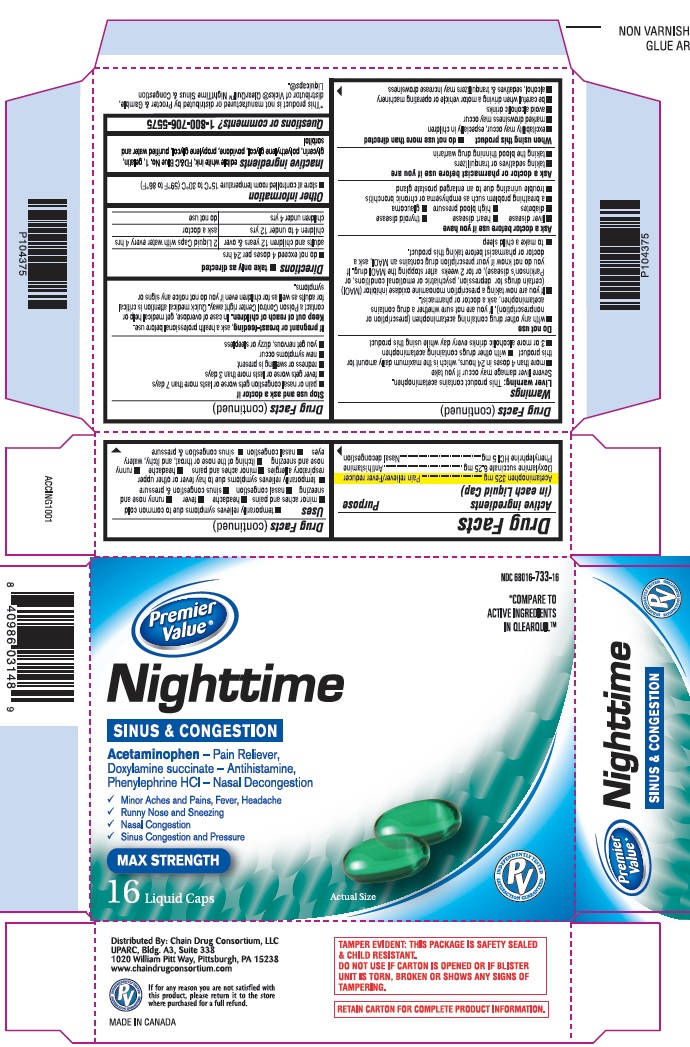 DRUG LABEL: Night Time Sinus and Congestion
NDC: 68016-733 | Form: CAPSULE, LIQUID FILLED
Manufacturer: Chain Drug Consortium, LLC
Category: otc | Type: HUMAN OTC DRUG LABEL
Date: 20151012

ACTIVE INGREDIENTS: ACETAMINOPHEN 325 mg/1 1; DOXYLAMINE SUCCINATE 6.25 mg/1 1; PHENYLEPHRINE HYDROCHLORIDE 5 mg/1 1
INACTIVE INGREDIENTS: FD&C BLUE NO. 1; GELATIN; GLYCERIN; POLYETHYLENE GLYCOLS; POVIDONE K12; PROPYLENE GLYCOL; WATER; SORBITOL

Drug Facts

Active ingredient(s)

Acetaminophen 325 mg

Doxylamine succinate 6.25 mg

Phenylephrine HCl 5 mg

Purpose

Pain reliever/Fever reducer

Antihistamine

Nasal decongestion

Uses

- temporarily relieves symptoms due to common cold
- minor aches and pains
- headache
- fever
- runny nose and sneezing
- nasal congestion
- sinus congestion & pressure
- temporarily relieves symptoms due to hay fever or other upper respiratory allergies
- minor aches and pains
- headache
- runny nose and sneezing
- itching of the nose or throat, and itchy, watery eyes
- nasal congestion
- sinus congestion & pressure

Warnings

Liver warning: This product contains acetaminophen.

Severe liver damage may occur if you take

- more than 4 doses in 24 hours, which is the maximum daily amount for this product
- with other drugs containing acetaminophen
- 3 or more alcoholic drinks every day while using this product

Do not use

- with any other drug containing acetaminophen (prescription or nonprescription). If you are not sure whether a drug contains acetaminophen, ask a doctor or pharmacist.
- If you are now taking a prescription monoamine oxidase inhibitor (MAOI) (certain drugs for depression, psychiatric or emotional conditions, or Parkinson’s disease), or for 2 weeks after stopping the MAOI drug. If you do not know if your prescription drug contains an MAOI, ask a doctor or pharmacist before taking this product.
- to make a child sleep

Ask a doctor before use if

- liver disease
- heart disease
- thyroid disease
- diabetes
- high blood pressure
- glaucoma
- a breathing problem such as emphysema or chronic bronchitis
- trouble urinating due to an enlarged prostate gland

Ask a doctor or pharmacist before use ifyou are

- taking sedatives or tranquilizers
- taking the blood thinning drug warfarin

When using this product

- do not use more than directed
- excitability may occur, especially in children
- marked drowsiness may occur
- avoid alcoholic drinks
- be careful when driving a motor vehicle or operating machinery
- alcohol, sedatives & tranquilizers may increase drowsiness

Stop use and ask doctor if

- pain or nasal congestion gets worse or lasts more than 7 days
- fever gets worse or lasts more than 3 days
- redness or swelling is present
- new symptoms occur
- you get nervous, dizzy or sleepless

If pregnant or breast-feeding,

ask a health professional before use.

Keep out of reach of children.

In case of overdose, get medical help or contact a Poison Control Center right away. Quick medical attention is critical for adults as well as for children even if you do not notice any signs or symptoms.

Directions

- take only as directed
- take only as directed

adults & children 12 years & over | 2 Liquid Caps with water every 4 hrs
children 4 to under 12 yrs | ask a doctor
children under 4 yrs | do not use

Other information

- store at controlled room temperature 15°C to 30°C (59°F to 86°F)

Inactive ingredients

edible white ink, FD&C Blue No. 1, gelatin, glycerin, polyethylene glycol, povidone, propylene glycol, purified water and sorbitol

Questions or comments?

1-800-706-5575

Principal Display Panel

Premier Value

Nighttime Sinus and Congestion

NDC number 68016-733-16

16 Liquid Capsule